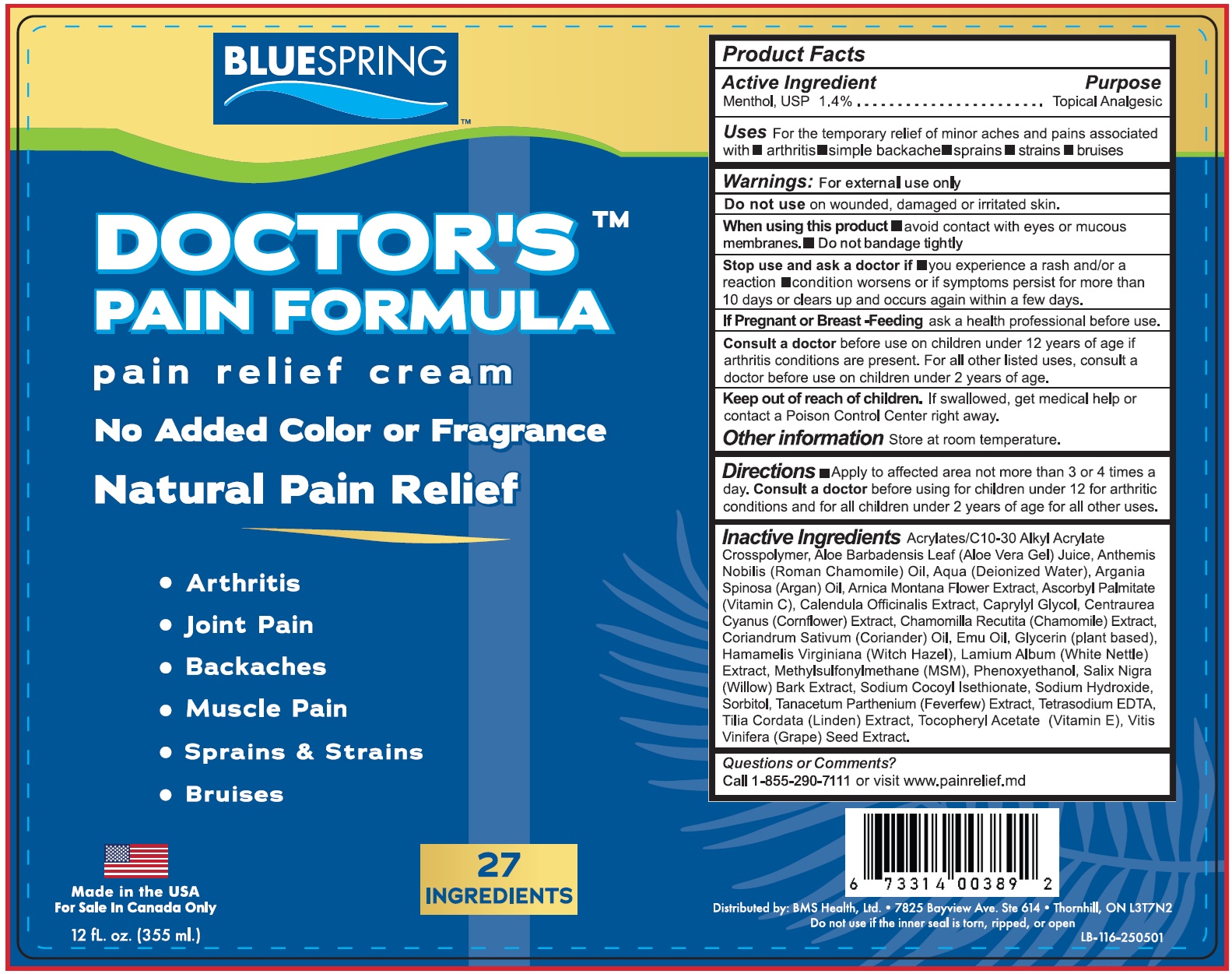 DRUG LABEL: BLUESPRING Doctors Pain Formula Pain Relief
NDC: 83591-629 | Form: CREAM
Manufacturer: ACA MANAGEMENT LLC
Category: otc | Type: HUMAN OTC DRUG LABEL
Date: 20250714

ACTIVE INGREDIENTS: MENTHOL 14 mg/1 mL
INACTIVE INGREDIENTS: ALOE VERA LEAF; WATER; ARGAN OIL; ARNICA MONTANA FLOWER; ASCORBYL PALMITATE; CALENDULA OFFICINALIS FLOWER; CAPRYLYL GLYCOL; CHAMOMILE; CORIANDER; EMU OIL; GLYCERIN; WITCH HAZEL; DIMETHYL SULFONE; PHENOXYETHANOL; SALIX NIGRA BARK; SODIUM COCOYL ISETHIONATE; SODIUM HYDROXIDE; SORBITOL; FEVERFEW; EDETATE SODIUM; TILIA CORDATA WHOLE; .ALPHA.-TOCOPHEROL ACETATE; VITIS VINIFERA SEED

BLUESPRING Doctor's Pain Formula Pain Relief Cream

Active Ingredient

Menthol, USP 1.4%

Purpose

Topical Analgesic

Uses

For the temporary relief of minor aches and pains associated with • arthritis • simple backache • sprains • strains • bruises

Warnings:

For external use only

Do not use

on wounded, damaged or irritated skin.

When using this product

- avoid contact with eyes or mucous membranes.
- Do not bandage tightly

Stop use and ask a doctor if

- you experience a rash and/or a reaction
- condition worsens or if symptoms persist for more than 10 days or clear up and occur again within few days.

If Pregnant or Breast-Feeding

ask a health professional before use. Consult a doctorbefore use on children under 12 years of age if arthritis conditions are present. For all other listed uses, consult a doctor before use on children under 2 years of age.

Keep out of reach of children.

If swallowed, get medical help or contact a Poison Control Center right away.

Other information

Store at room temperature.

Directions

- Apply to affected area not more than 3 or 4 times a day. Consult a doctorbefore using for children under 12 for arthritic conditions and for all children under 2 years of age for all other uses.

Inactive Ingredients

Acrylates/C10-30 Alkyl Acrylate Crosspolymer, Aloe Barbadensis Leaf (Aloe Vera Gel) Juice, Anthemis Nobilis (Roman Chamomile) Oil, Aqua (Deionized Water), Argania Spinosa (Argan) Oil, Arnica Montana Flower Extract, Ascorbyl Palmitate (Vitamin C), Calendula Officinalis Extract, Caprylyl Glycol, Centaurea Cyanus (Cornflower) Extract, Chamomilla Recutita (Chamomile) Extract, Coriandrum Sativum (Coriander) Oil, Emu Oil, Glycerin (plant based), Hamamelis Virginiana (Witch Hazel), Lamium Album (White Nettle) Extract, Methylsulfonylmethane (MSM), Phenoxyethanol, Salix Nigra (Willow) Bark Extract, Sodium Cocoyl Isethionate, Sodium Hydroxide, Sorbitol, Tanacetum Parthenium (Feverfew) Extract, Tetrasodium EDTA, Tilia Cordata (Linden) Extract, Tocopheryl Acetate (Vitamin E), Vitis Vinifera (Grape) Seed Extract.

Questions or Comments?

Call 1-855-290-7111or visit www.painrelief.md